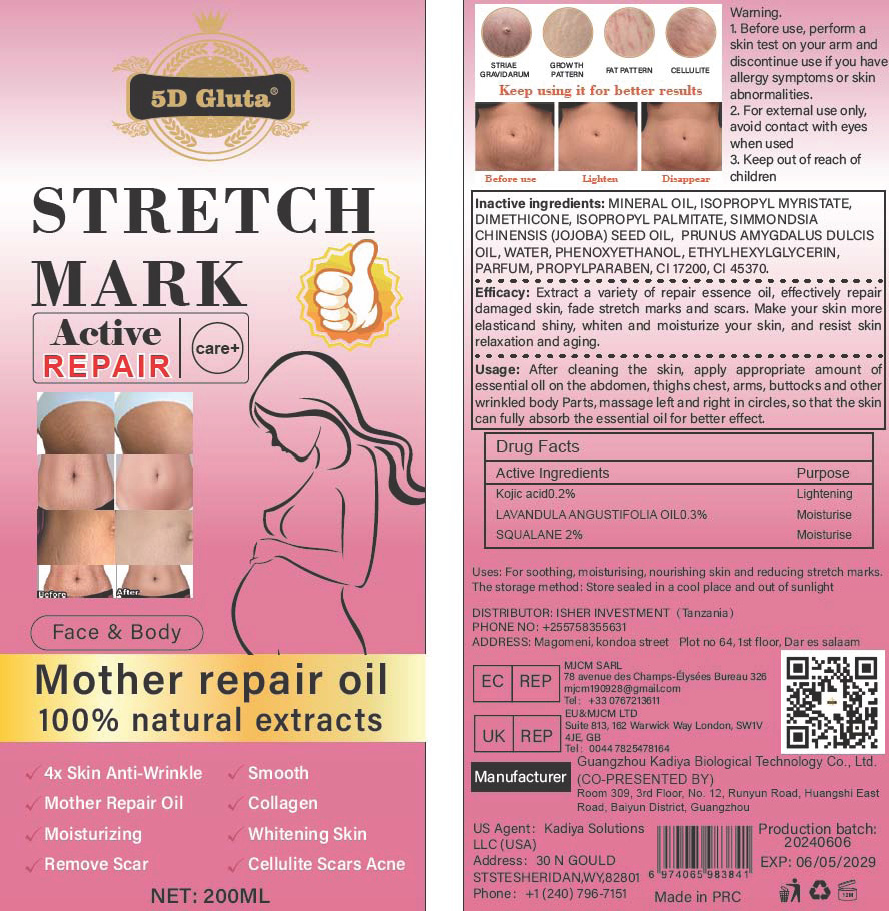 DRUG LABEL: Motherrepairoil
NDC: 84423-050 | Form: EXTRACT
Manufacturer: Guangzhou Kadiya Biotechnology Co., Ltd.
Category: otc | Type: HUMAN OTC DRUG LABEL
Date: 20240928

ACTIVE INGREDIENTS: SQUALANE 4 g/200 mL; LAVENDER OIL 0.6 g/200 mL; KOJIC ACID 0.4 g/200 mL
INACTIVE INGREDIENTS: D&C RED NO. 33; PROPYLPARABEN; ISOPROPYL MYRISTATE; ISOPROPYL PALMITATE; ALMOND OIL; PHENOXYETHANOL; ETHYLHEXYLGLYCERIN; MINERAL OIL; DIMETHICONE; JOJOBA OIL; WATER; SOLVENT RED 72

PURPOSE

For soothing, moisturising, nourishing skin and reducing stretch marks.

INACTIVE INGREDIENT

MINERAL OIL，ISOPROPYL MYRISTATE，DIMETHICONE，ISOPROPYL PALMITATE，SIMMONDSIA CHINENSIS (JOJOBA) SEED OIL， PRUNUS AMYGDALUS DULCIS OIL，WATER，PHENOXYETHANOL，ETHYLHEXYLGLYCERIN，PARFUM，PROPYLPARABEN，CI 17200，CI 45370

Warning.
1.Before use, perform a skin test on your arm and discontinue use if you have allergy symptoms or skin abnormalities.
2、For external use only, avoid contact with eyes when used
3、Keep out of reach of children

INDICATIONS AND USAGE

Extract a variety of repair essence oil, effectively repair damaged skin, fade stretch marks and scars. Make your skin more elasticand shiny, whiten and moisturize your skin, and resist skin relaxation and aging.

DOSAGE AND ADMINISTRATION

After cleaning the skin, apply appropriate amount ofessential oll on the abdomen, thighs chest, arms, buttocks and otherwrinkled body Parts, massage left and right in circles, so that the skincan fully absorb the essential oil for better effect.

KEEP OUT OF REACH OF CHILDREN SECTION

Active Ingredients
Kojic acid0.2%
LAVANDULA ANGUSTIFOLIA OIL0.3%
SQUALANE 2%

Drug Facts
Active Ingredients
Kojic acid0.2%
LAVANDULA ANGUSTIFOLIA OIL0.3%
SQUALANE 2%

Uses：
For soothing, moisturising, nourishing skin and reducing stretch marks.
The storage method：
Store sealed in a cool place and out of sunlight

Warning.
1.Before use, perform a skin test on your arm and discontinue use if you have allergy symptoms or skin abnormalities.
2、For external use only, avoid contact with eyes when used
3、Keep out of reach of children

Inactive ingredients：
MINERAL OIL，ISOPROPYL MYRISTATE，DIMETHICONE，ISOPROPYL PALMITATE，SIMMONDSIA CHINENSIS (JOJOBA) SEED OIL， PRUNUS AMYGDALUS DULCIS OIL，WATER，PHENOXYETHANOL，ETHYLHEXYLGLYCERIN，PARFUM，PROPYLPARABEN，CI 17200，CI 45370